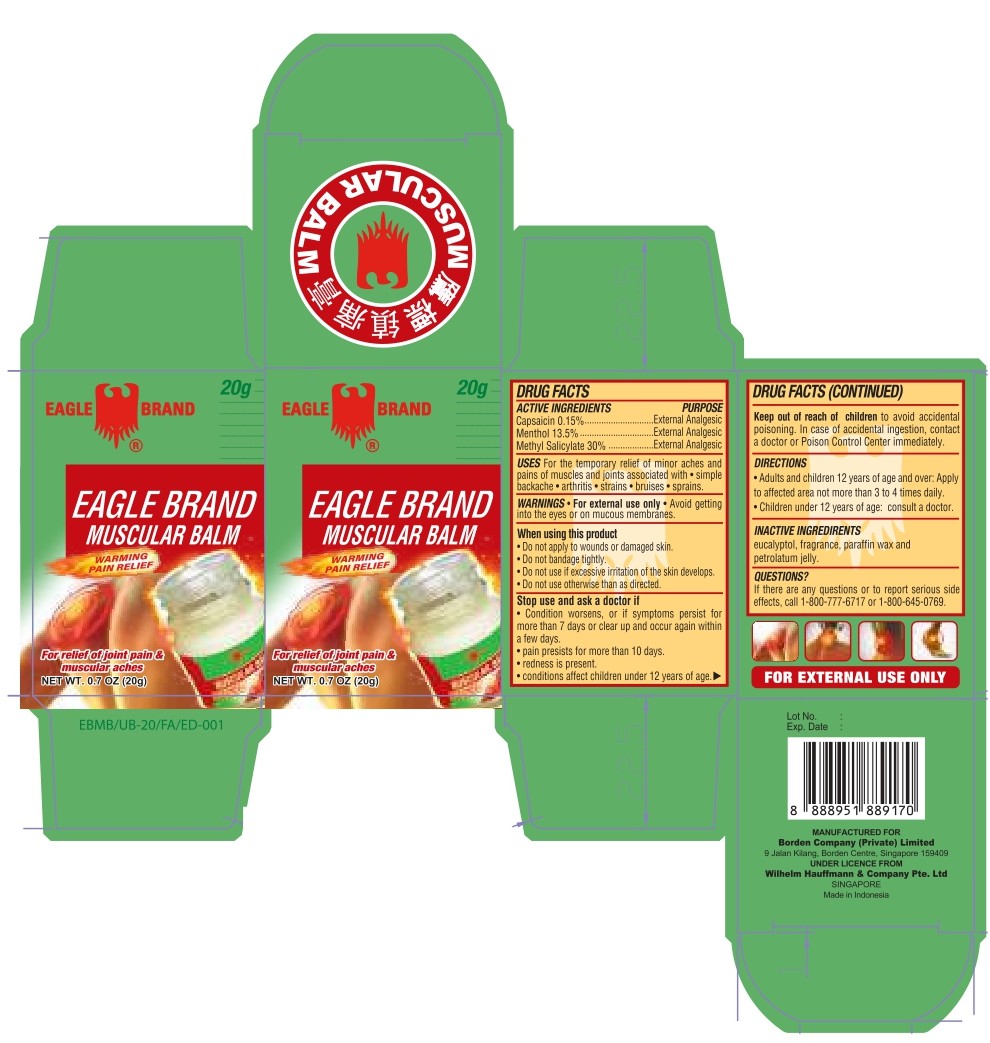 DRUG LABEL: Muscular Balm
NDC: 60954-001 | Form: OINTMENT
Manufacturer: Eagle Indo Pharma, PT
Category: otc | Type: HUMAN OTC DRUG LABEL
Date: 20260202

ACTIVE INGREDIENTS: CAPSAICIN 0.15 g/100 g; MENTHOL 13.5 g/100 g; METHYL SALICYLATE 30 g/100 g
INACTIVE INGREDIENTS: EUCALYPTOL; PARAFFIN; PETROLATUM

Drug Facts

Active Ingredients

Capsaicin 0.15%
Menthol 13.5%
Methyl Salicylate 30%

Purpose

External Analgesic

External Analgesic

External Analgesic

Uses

For the temporary relief of minor pains and aches of muscles and joints associated with ■ simple backache ■ arthritis

■ strains ■ bruises ■ sprains

Warnings

■ For external use only

■ Avoid getting into the eyes or on mucus membranes.

When using this product

■ do not apply to wound or damaged skin ■ do not bandage tightly ■ do not use if excessive irritation of the skin develops

■ do not use otherwise than as directed.

Stop use and ask a doctor if

■ condition worsens, or if symptoms persist for more than 7 days or clear up and occur again within a few days ■ pain persists for more than 10 days ■ redness is present ■ conditions affect children under 12 years of age

Keep out of reach of children

to avoid accidental poisoning. In case of accidental ingestion, contact a doctor or Poison Control Center Immediately

Directions

■ Adults and children 12 years of age and over: Apply to affected area not more than 3 to 4 time daily ■ Children under 12 years of age:consult a doctor

Inactive Ingredients

eucalyptol, fragrance, paraffin wax and petroleum jelly

Package Label

20g NDC: 60954-001-01